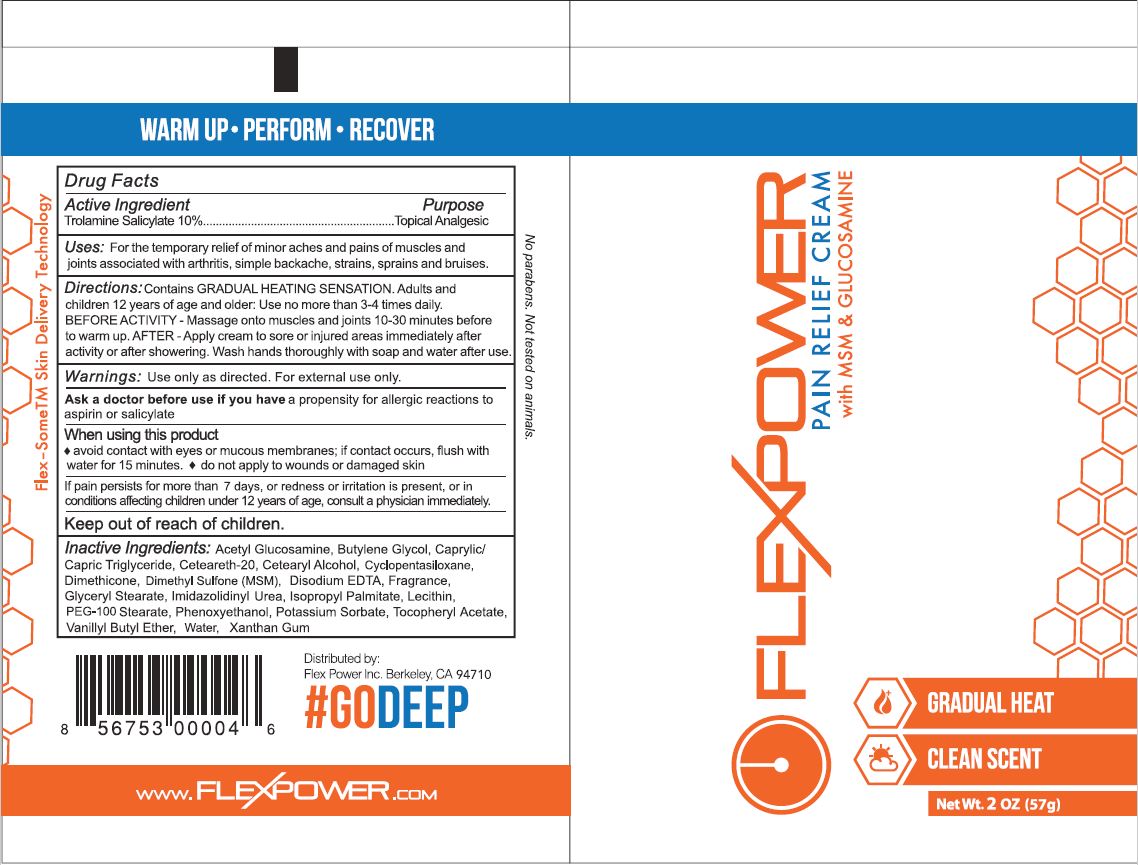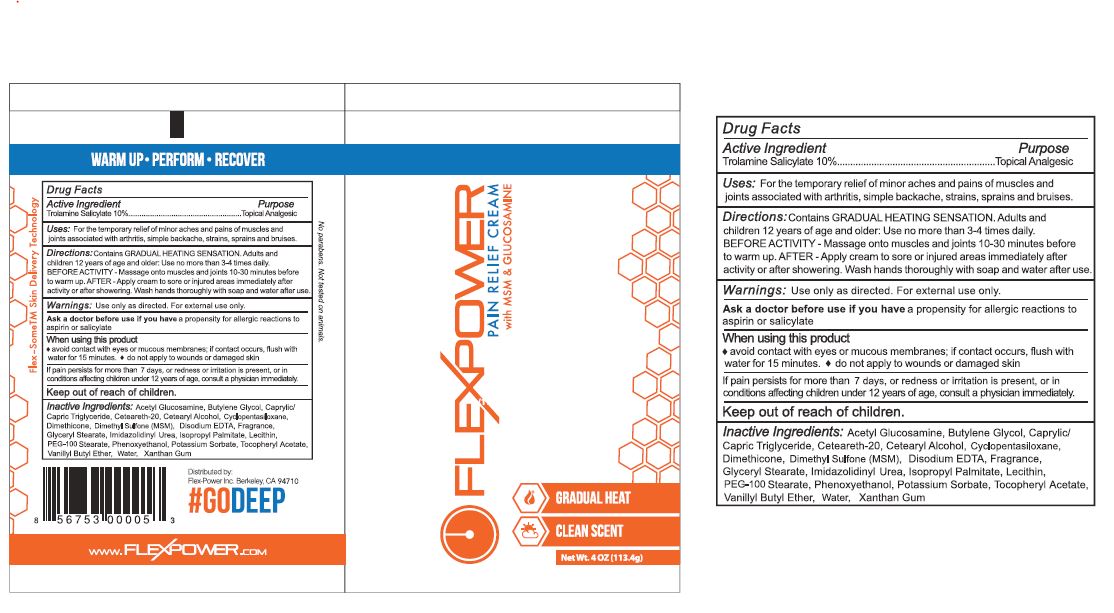 DRUG LABEL: Pain Relief Cream
NDC: 62742-4091 | Form: CREAM
Manufacturer: ALLURE LABS INC.
Category: otc | Type: HUMAN OTC DRUG LABEL
Date: 20171127

ACTIVE INGREDIENTS: TROLAMINE SALICYLATE 100 mg/1 g
INACTIVE INGREDIENTS: DISODIUM ACETYL GLUCOSAMINE PHOSPHATE; BUTYLENE GLYCOL; CETEARETH-2; DIMETHICONE CROSSPOLYMER (450000 MPA.S AT 12% IN CYCLOPENTASILOXANE); DIMETHICONE; DIMETHYL SULFONE; EDETATE DISODIUM; GLYCERYL STEARATE CITRATE; N-(1,3-BIS(HYDROXYMETHYL)-2,5-DIOXO-4-IMIDAZOLIDINYL)-N,N'-BIS(HYDROXYMETHYL)UREA; ISOPROPYL PALMITATE; LECITHIN, SOYBEAN; PEG-100 STEARATE; PHENOXYETHANOL; VANILLYL BUTYL ETHER; WATER; XANTHAN GUM; TOCOPHEROL; MEDIUM-CHAIN TRIGLYCERIDES

DRUG FACTS

Active Ingredients:

Trolamine Salicylate - 10%

Purpose:

Topical Analgesic

INDICATIONS AND USAGE

Uses: For the temporary relief of minor aches and pains of muscles and joints associated with arthritis, simple backache, strains, sprains and bruises.

WARNINGS

For external use only.

Ask a doctor before use if you have a propensity for allergic reactions to aspirin or salicylate.

When using this product: Avoid contact with eyes or mucous membranes; if contacts occurs, flush with water for 15 minutes. Do not apply to wounds or damaged skin.

STOP USE

If pain persist more than 7 days or redness or irritation is present or in condition affecting children under 12 years of age, consult a physician immediately.

Keep out of reach of children.

Inactive ingredients

Acetyl Glucosamine, Butylene Glycol, Capriylic/ Capric Triglyceride, Ceteareth-20, Cetearyl Alcohol,Cyclopentasilaxane, Dimethicone, Dimethyl Sulfone (MSM), Disodium EDTA, Fragrance, Glyceryl Stearate, Imidazolidinyl Uraea, Isopropyl Palmitate, Lecithine, PEG-100 Stearate, Phenoxy ethanol, Potassium Sorbitate, Tocopheryl Acetate, Vanillyl Butyl Ethar, Water, Xanthan Gum.

DOSAGE AND ADMINISTRATION

Contains Gradual Heating Sensation. Adults and Children 12 years of age and older: use no more than 3-4 times daily. Before Activity-Massage onto muscles and joints 10-30 minutes before to warm up. After - Apply cream to sore or injured areas immediately after activity or after showering. Wash hands thoroughly with soap and water after use

PACKAGE LABEL

Distributed by:

Flex Power Inc.

Berkeley, CA 94710